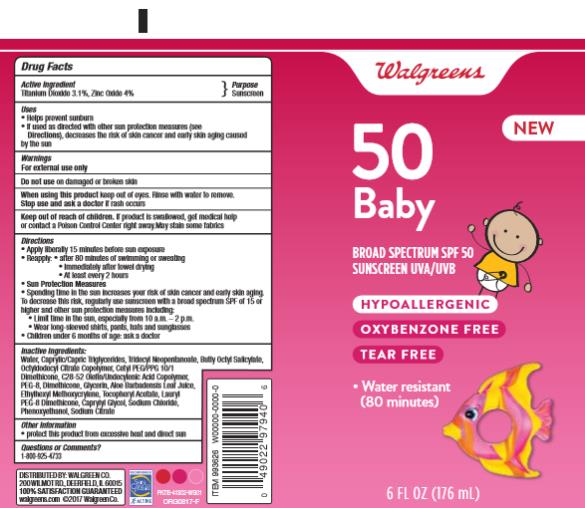 DRUG LABEL: Walgreens Baby SPF50
NDC: 0363-9936 | Form: LOTION
Manufacturer: Walgreen Company
Category: otc | Type: HUMAN OTC DRUG LABEL
Date: 20170830

ACTIVE INGREDIENTS: TITANIUM DIOXIDE 3.1 mg/100 mg; ZINC OXIDE 4 mg/100 mg
INACTIVE INGREDIENTS: WATER; MEDIUM-CHAIN TRIGLYCERIDES; TRIDECYL NEOPENTANOATE; SORBITOL; CETYL PEG/PPG-10/1 DIMETHICONE (HLB 3); BUTYLOCTYL SALICYLATE; GLYCERIN; POLYOXYL 8 STEARATE; DIMETHICONE; ALOE VERA LEAF; ETHYLHEXYL METHOXYCRYLENE; ALPHA-TOCOPHEROL ACETATE; LAURYL PEG/PPG-18/18 METHICONE; CAPRYLYL GLYCOL; SODIUM CHLORIDE; PHENOXYETHANOL; SODIUM CITRATE

WAG Sun Baby Lotion SPF50 6oz

1491-23(V) Rev 01

Walgreen Baby SPF 50 Lotion

Active Ingredients

Titanium Oxide 3.30%, Zinc Oxide 4.2%

Purpose

Sunscreen

Uses

- helps prevent sunburn
- if used as directed with other sun protection measures (see Directions), decreases the risk of skin cancer and early skin aging caused by the sun

Warnings

For external use only

Do not use

on damaged or broken skin

When using this product

keep out of eyes. Rinse with water to remove.

Stop use and ask a doctor

if rash occurs

Keep out of reach of children.

If swallowed, get medical help or contact a Poison Control Center right away.

Directions

- apply liberally 15 minutes before sun exposure
- reapply:
  ● after 80 minutes of swimming or sweating
  ● immediately after towel drying
  ● at least every 2 hours
- Sun Protection Measures. Spending time in the sun increases your risk of skin cancer and early skin aging. To decrease this risk, regularly use a sunscreen with a Broad Spectrum SPF of 15 or higher and other sun protection measures including:
  ● limit time in the sun, especially from 10 a.m. - 2 p.m.
  ● wear long-sleeve shirts, pants, hats, and sunglasses
- children under 6 months: Ask a doctor

Inactive Ingredients

Deionized Water, Caprylic/Capric Triglycerides, Tridecyl Neopentanoate, Sorbitol, Cetyl PEG/PPG 10/1 Dimethicone, Butly Octyl Salicylate, Glycerin, Octyldodecyl Citrate Copolymer, C28-52 Olefin/Undecylenic Acid Copolymer, PEG 8, Dimethicone, Aloe Barbadensis Leaf Juice, Ethylhexyl Methoxycrylene, Tocopherol Acetate, Lauryl PEG-8 Dimethicone, Caprylyl Glycol, Sodium Chloride, Phenoxyethanol, Sodium Citrate

Other Information

- for use on skin only. Avoid contact with fabric
- protect this product from excessive heat and direct sun

Questions or comments?

www.walgreens.com or call toll free 1-800-XX-XXXX

PRINCIPAL DISPLAY PANEL

Walgreens
50
Baby
Broad spectrum SPF 50
Sunscreen UVA/UVB
HYPOALLERGENIC
OXYBENZONE FREE
TEAR FREE
6 FL OZ (176 m L)